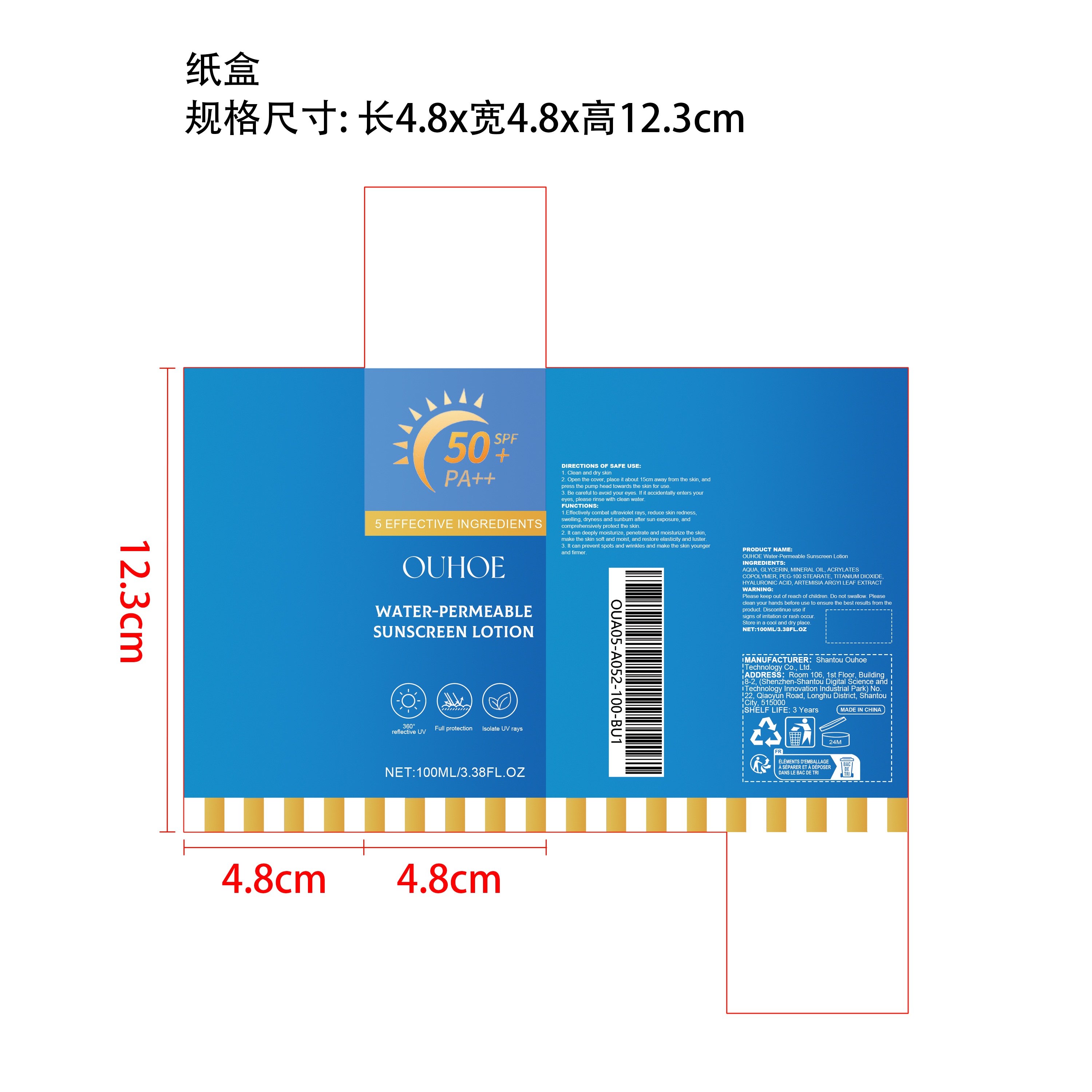 DRUG LABEL: OUHOE Water-Permeable Sunscreen
NDC: 85163-019 | Form: SPRAY
Manufacturer: Shantou Ouhoe Technology Co., Ltd.
Category: otc | Type: HUMAN OTC DRUG LABEL
Date: 20251226

ACTIVE INGREDIENTS: ARTEMISIA ARGYI LEAF 0.01 mg/100 mg
INACTIVE INGREDIENTS: TITANIUM DIOXIDE 1 mg/100 mg; PEG-100 STEARATE 2 mg/100 mg; HYALURONIC ACID 0.02 mg/100 mg; GLYCERIN 3 mg/100 mg; ACRYLATES CROSSPOLYMER-6 2 mg/100 mg; AQUA 88.97 mg/100 mg; MINERAL OIL 3 mg/100 mg

ACTIVE INGREDIENT

ARTEMISIA ARGYI LEAF EXTRACT

PURPOSE

1.Effectively combat ultraviolet rays, reduce skin redness, swelling, dryness and sunburn after sun exposure, and comprehensively protect the skin.

2. It can deeply moisturize, penetrate and moisturize the skin, make the skin soft and moist, and restore elasticity and luster.

3. It can prevent spots and wrinkles and make the skin younger and firmer.

WHEN USING

1. Clean and dry skin

2. Open the cover, place it about 15cm away from the skin, and press the pump head towards the skin for use.

3. Be careful to avoid your eyes. If it accidentally enters your eyes, please rinse with clean water.

WARNINGS

Please keep out of reach of children. Do not swallow.Please clean your hands before use to ensure the best results from the product. Discontinue use if signs of irritation or rash occur. Store in a cool and dry place.

DO NOT USE

Discontinue use if signs of irritation or rash occur.

STOP USE

Discontinue use if signs of irritation or rash occur.

KEEP OUT OF REACH OF CHILDREN

Please keep out of reach of children. Do not swallow.

STORAGE AND HANDLING

Store in a cool and dry place.

INACTIVE INGREDIENT

AQUA、GLYCERIN、MINERAL OIL、ACRYLATES COPOLYMER、PEG-100 STEARATE、TITANIUM DIOXIDE、HYALURONIC ACID

DOSAGE AND ADMINISTRATION

1. Clean and dry skin

2. Open the cover, place it about 15cm away from the skin, and press the pump head towards the skin for use.

3. Be careful to avoid your eyes. If it accidentally enters your eyes, please rinse with clean water.

INDICATIONS AND USAGE

1. Clean and dry skin

2. Open the cover, place it about 15cm away from the skin, and press the pump head towards the skin for use.

3. Be careful to avoid your eyes. If it accidentally enters your eyes, please rinse with clean water.